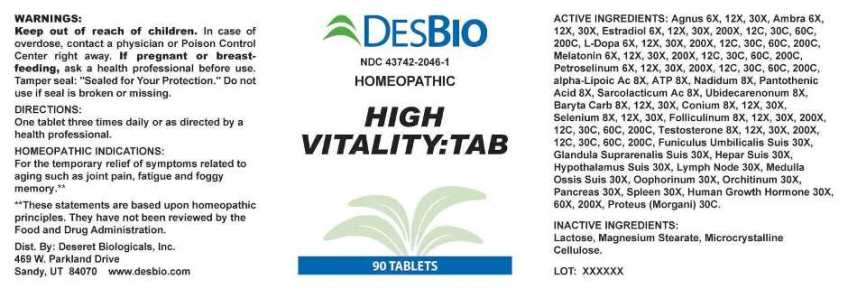 DRUG LABEL: High Vitality Tab
NDC: 43742-2046 | Form: TABLET
Manufacturer: Deseret Biologicals
Category: homeopathic | Type: HUMAN OTC DRUG LABEL
Date: 20231212
DEA Schedule: CIII

ACTIVE INGREDIENTS: CHASTE TREE FRUIT 6 [hp_X]/1 1; AMBERGRIS 6 [hp_X]/1 1; ESTRADIOL 6 [hp_X]/1 1; LEVODOPA 6 [hp_X]/1 1; MELATONIN 6 [hp_X]/1 1; PETROSELINUM CRISPUM WHOLE 6 [hp_X]/1 1; ADENOSINE TRIPHOSPHATE DISODIUM 8 [hp_X]/1 1; ALPHA LIPOIC ACID 8 [hp_X]/1 1; NADIDE 8 [hp_X]/1 1; PANTOTHENIC ACID 8 [hp_X]/1 1; LACTIC ACID, L- 8 [hp_X]/1 1; UBIDECARENONE 8 [hp_X]/1 1; BARIUM CARBONATE 8 [hp_X]/1 1; CONIUM MACULATUM FLOWERING TOP 8 [hp_X]/1 1; SELENIUM 8 [hp_X]/1 1; ESTRONE 8 [hp_X]/1 1; TESTOSTERONE 8 [hp_X]/1 1; SUS SCROFA UMBILICAL CORD 30 [hp_X]/1 1; SUS SCROFA ADRENAL GLAND 30 [hp_X]/1 1; PORK LIVER 30 [hp_X]/1 1; SUS SCROFA HYPOTHALAMUS 30 [hp_X]/1 1; SUS SCROFA LYMPH 30 [hp_X]/1 1; SUS SCROFA BONE MARROW 30 [hp_X]/1 1; SUS SCROFA OVARY 30 [hp_X]/1 1; SUS SCROFA TESTICLE 30 [hp_X]/1 1; SUS SCROFA PANCREAS 30 [hp_X]/1 1; SUS SCROFA SPLEEN 30 [hp_X]/1 1; SOMATROPIN 30 [hp_X]/1 1; PROTEUS MORGANII 30 [hp_C]/1 1
INACTIVE INGREDIENTS: LACTOSE MONOHYDRATE; MAGNESIUM STEARATE; CELLULOSE, MICROCRYSTALLINE

DRUG FACTS:

ACTIVE INGREDIENTS:

Agnus Castus 6X, 12X, 30X, Ambra Grisea 6X, 12X, 30X, Estradiol 6X, 12X, 30X, 200X, 12C, 30C, 60C, 200C, L-Dopa 6X, 12X, 30X, 200X, 12C, 30C, 60C, 200C, Melatonin 6X, 12X, 30X, 200X, 12C, 30C, 60C, 200C, Petroselinum Sativum 6X, 12X, 30X, 200X, 12C, 30C, 60C, 200C, Adenosinum Triphosphoricum Disodium 8X, Alpha-Lipoicum Acidum 8X, Nadidum 8X, Pantothenic Acid 8X, Sarcolacticum Acidum 8X, Ubidecarenonum 8X, Baryta Carbonica 8X, 12X, 30X, Conium Maculatum 8X, 12X, 30X, Selenium Metallicum 8X, 12X, 30X, Folliculinum 8X, 12X, 30X, 200X, 12C, 30C, 60C, 200C, Testosterone 8X, 12X, 30X, 200X, 12C, 30C, 60C, 200C, Funiculus Umbilicalis Suis 30X, Glandula Suprarenalis Suis 30X, Hepar Suis 30X, Hypothalamus (Suis) 30X, Lymph Node (Suis) 30X, Medulla Ossis Suis 30X, Oophorinum (Suis) 30X, Orchitinum (Suis) 30X, Pancreas Suis 30X, Spleen (Suis) 30X, Human Growth Hormone 30X, 60X, 200X, Proteus (Morgani) 30C.

HOMEOPATHIC INDICATIONS:

For the temporary relief of symptoms related to aging such as joint pain, fatigue and foggy memory.**

**These statements are based upon homeopathic principles. They have not been reviewed by the Food and Drug Administration.

WARNINGS:

Keep out of reach of children. In case of overdose, contact a physician or Poison Control Center right away.

If pregnant or breast-feeding, ask a health professional before use.

Tamper seal: "Sealed for Your Protection." Do not use if seal is broken or missing.

Keep out of reach of children. In case of overdose, contact a physician or Poison Control Center right away.

DIRECTIONS:

One tablet three times daily or as directed by a health professional.

HOMEOPATHIC INDICATIONS:

For the temporary relief of symptoms related to aging such as joint pain, fatigue and foggy memory.**

**These statements are based upon homeopathic principles. They have not been reviewed by the Food and Drug Administration.

INACTIVE INGREDIENTS:

Lactose, Magnesium Stearate, Microcrystalline Cellulose.

QUESTIONS:

Dist. By: Deseret Biologicals, Inc.

469 W. Parkland Drive

Sandy, UT 84070 www.desbio.com

PACKAGE LABEL DISPLAY:

DESBIO

NDC 43742-2046-1

HOMEOPATHIC

HIGH VITALITY:TAB

90 TABLETS